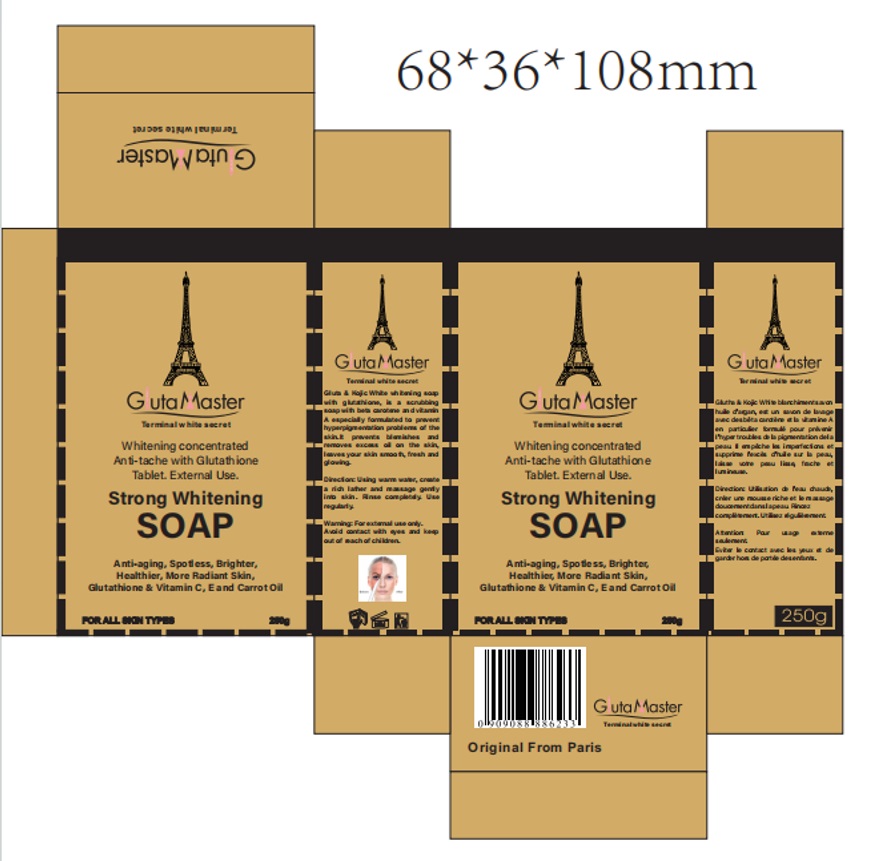 DRUG LABEL: StrongWhiteningSoap
NDC: 84423-053 | Form: SOAP
Manufacturer: Guangzhou Kadiya Biotechnology Co., Ltd.
Category: otc | Type: HUMAN OTC DRUG LABEL
Date: 20241217

ACTIVE INGREDIENTS: GLUTATHIONE 0.25 g/250 g; KOJIC ACID 0.25 g/250 g; BUTYROSPERMUM PARKII (SHEA) BUTTER UNSAPONIFIABLES 0.75 g/250 g; OLEA EUROPAEA (OLIVE) FRUIT OIL 1.25 g/250 g; CHARCOAL POWDER 0.25 g/250 g
INACTIVE INGREDIENTS: MANNITOL; METHYL ALCOHOL; MALTITOL; WATER; SUCROSE; SODIUM LAURETH SULFATE; PROPYLENE GLYCOL; COCOS NUCIFERA (COCONUT) OIL; LAURIC ACID; GLYCERIN; SODIUM HYDROXIDE; SORBITOL; COCAMIDOPROPYL BETAINE; STEARIC ACID

PURPOSE

For facial skin cleansing, exfoliation and whitening moisturization

INACTIVE INGREDIENT

WATER、STEARIC ACID、SORBITOL、WHITE SUGAR、SODIUM、
LAURETH SULFATE、LAURIC ACID、GLYCERIN、PROPYLENE GLYCOL、SODIUM HYDROXIDE、MALTITOL、COCAMIDOPYOPY IBETAINE、COCOS NUCIFERA(COCONUT)OIL、MANNITOL、ETHYL ALCOHOL

WARNINGS

1、For external use only, avoid contact with eyes when used
2、Keep out of reach of children

INDICATIONS AND USAGE

Anti-aging, Spotless, Brighter, Healthier, More Radiant Skin, Glutathione & Vitamin C, Eand CarrotOil

DOSAGE AND ADMINISTRATION

External use

KEEP OUT OF REACH OF CHILDREN SECTION

Active Ingredients Purpose
Glutathione0.1% Whitening
KOJIC ACID0.1% Whitening
CHARCOAL POWDER0.1% Cleansing
OLEA EUROPAEA FRUIT EXTRACT0.5% Moisturize
BUTYROSPERMUM PARKII BUTTER0.3% Nourish

PACKAGE LABEL

Active Ingredients
Glutathione0.1%
KOJIC ACID0.1%
CHARCOAL POWDER0.1%
OLEA EUROPAEA FRUIT EXTRACT0.5%
BUTYROSPERMUM PARKII BUTTER0.3%

Uses：
For facial skin cleansing, exfoliation and whitening moisturization

The storage method：
Store sealed in a cool place and out of sunlight

Warning.
1、For external use only, avoid contact with eyes when used
2、Keep out of reach of children

Inactive ingredients：
WATER、STEARIC ACID、SORBITOL、WHITE SUGAR、SODIUM、
LAURETH SULFATE、LAURIC ACID、GLYCERIN、PROPYLENE GLYCOL、SODIUM HYDROXIDE、MALTITOL、COCAMIDOPYOPY IBETAINE、AROMA、COCOS NUCIFERA(COCONUT)OIL、MANNITOL、ETHYL ALCOHOL